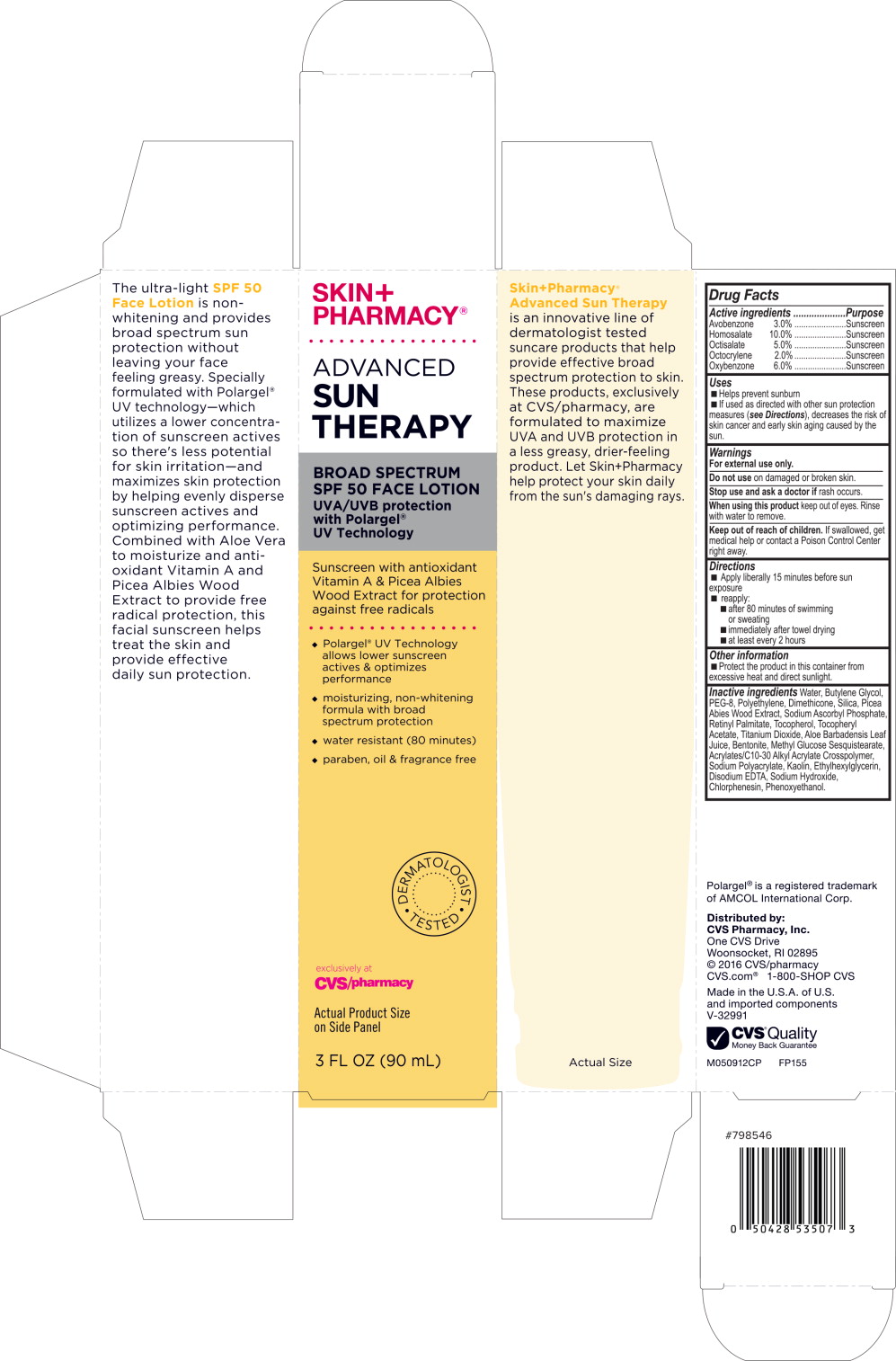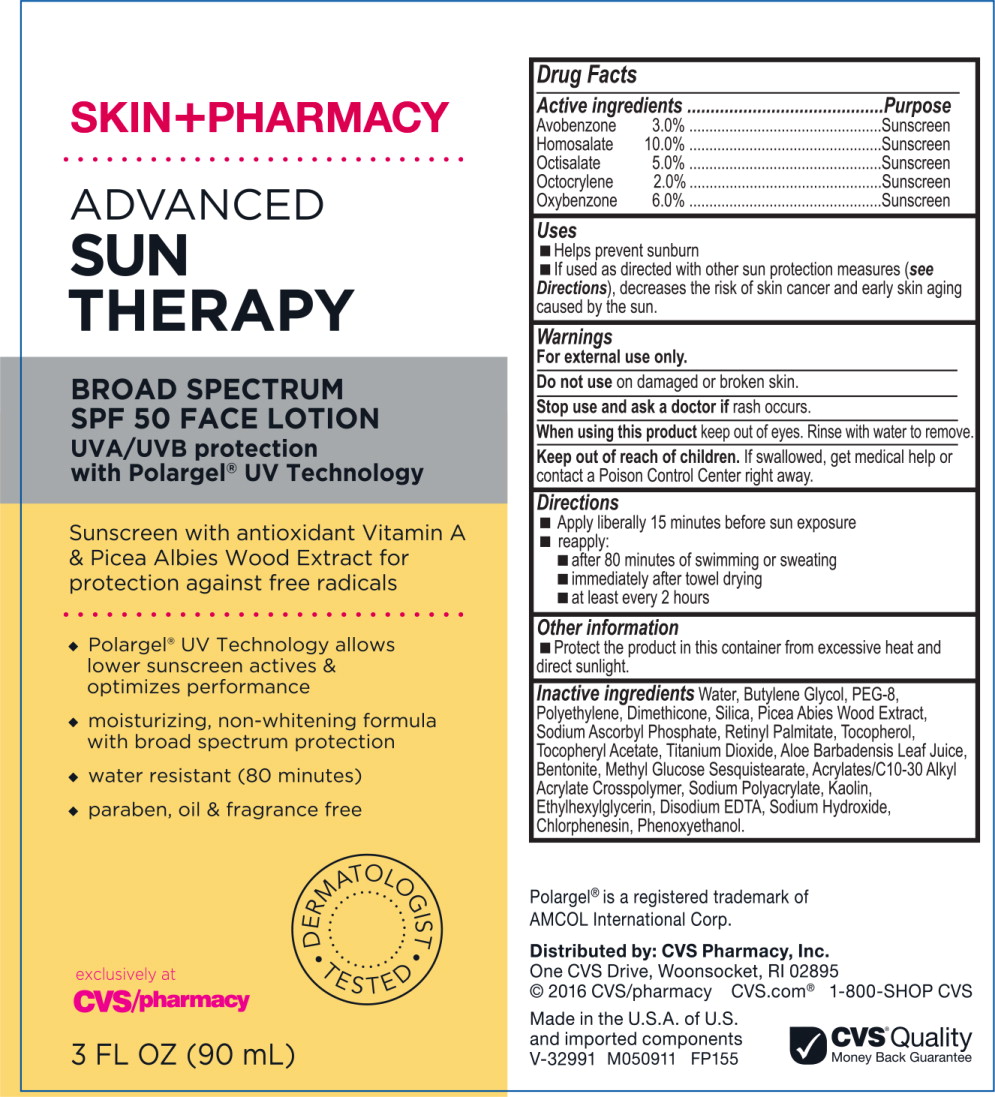 DRUG LABEL: SkinPharmacy Advanced Sun Therapy Broad Spectrum SPF 50 Face
NDC: 69842-021 | Form: LIQUID
Manufacturer: CVS Health
Category: otc | Type: HUMAN OTC DRUG LABEL
Date: 20170307

ACTIVE INGREDIENTS: homosalate 100 mg/1 mL; oxybenzone 60 mg/1 mL; octisalate 50 mg/1 mL; avobenzone 30 mg/1 mL; octocrylene 20 mg/1 mL
INACTIVE INGREDIENTS: water; butylene glycol; polyethylene glycol 400; high density polyethylene; dimethicone; silicon dioxide; picea abies wood; sodium ascorbyl phosphate; vitamin a palmitate; tocopherol; .alpha.-tocopherol acetate, DL-; titanium dioxide; aloe vera leaf; bentonite; carbomer copolymer type A; sodium polyacrylate (8000 mw); kaolin; ethylhexylglycerin; edetate disodium; sodium hydroxide; chlorphenesin; phenoxyethanol

Drug Facts

Active ingredients

Avobenzone 3.0%

Homosalate 10.0%

Octisalate 5.0%

Octocrylene 2.0%

Oxybenzone 6.0%

Purpose

Sunscreen

Sunscreen

Sunscreen

Sunscreen

Sunscreen

Uses

- Helps prevent sunburn
- If used as directed with other sun protection measures (see Directions), decreases the risk of skin cancer and early skin aging cause by the sun.

Warnings

For external use only.

Do not use on damaged or broken skin.

Stop use and ask a doctor if rash occurs.

When using this product keep out of eyes. Rinse with water to remove.

Keep out of reach of children. If swallowed, get medical help or contact a Poison Control Center right away.

Directions

- Apply liberally 15 minutes before sun exposure
- reapply:
  - after 80 minutes of swimming or sweating
  - immediately after towel drying
  - at least every 2 hours

Other information

- Protect the product in this container from excessive heat and direct sunlight.

Inactive ingredients

Water, Butylene Glycol, PEG-8, Polyethylene, Dimethicone, Silica, Picea Albies Wood Extract, Sodium Ascorbyl Phosphate, Retinyl Palmitate, Tocopherol, Tocopheryl Acetate, Titanium Dioxide, Aloe Barbadensis Leaf Juice, Bentonite, Methyl Glucose Sesquistearate, Acrylates/C10-30 Alkyl Acrylate Crosspolymer, Sodium Polyacrylate, Kaolin, Ethylhexylglycerin, Disodium EDTA, Sodium Hydroxide, Chlorphenesin, Phenoxyethanol.

Polargel® is a registered trademark of AMCOL International Corp.

Distributed by: CVS Pharmacy, Inc.
One CVS Drive, Woonsocket, RI 02895
© 2016 CVS/pharmacy
CVS.com® 1-800-SHOP CVS

Made in the U.S.A. of U.S. and imported components
V-32991

CVS® Quality
Money Back Guarantee

M050912CP FP155

Principal Display Panel - Carton Label

SKIN+
PHARMACY®

ADVANCED
SUN
THERAPY

BROAD SPECTRUM
SPF 50 FACE LOTION

UVA/UVB protection
with Polargel®
UV Technology

Sunscreen with antioxidant
Vitamin A & Picea Albies
Wood Extract for protection
against free radicals

♦ Polargel® UV Technology
  allows lower sunscreen
  actives & optimizes
  performance
♦ moisturizing, non-whitening
  formula with broad
  spectrum protection
♦ water resistant (80 minutes)
♦ paraben, oil & fragrance free

DERMATOLOGIST TESTED

exclusively at
CVS/pharmacy

Actual Product Size on Side Panel

3 FL OZ (90 mL)

Principal Display Panel - Tube Label

SKIN+PHARMACY®

ADVANCED
SUN
THERAPY

BROAD SPECTRUM
SPF 50 FACE LOTION

UVA/UVB protection
with Polargel® UV Technology

Sunscreen with antioxidant Vitamin A
& Picea Albies Wood Extract for
protection against free radicals

♦ Polargel® UV Technology allows
  lower sunscreen actives &
  optimizes performance
♦ moisturizing, non-whitening formula
  with broad spectrum protection
♦ water resistant (80 minutes)
♦ paraben, oil & fragrance free

DERMATOLOGIST TESTED

exclusively at

CVS/pharmacy

3 FL OZ (90 mL)